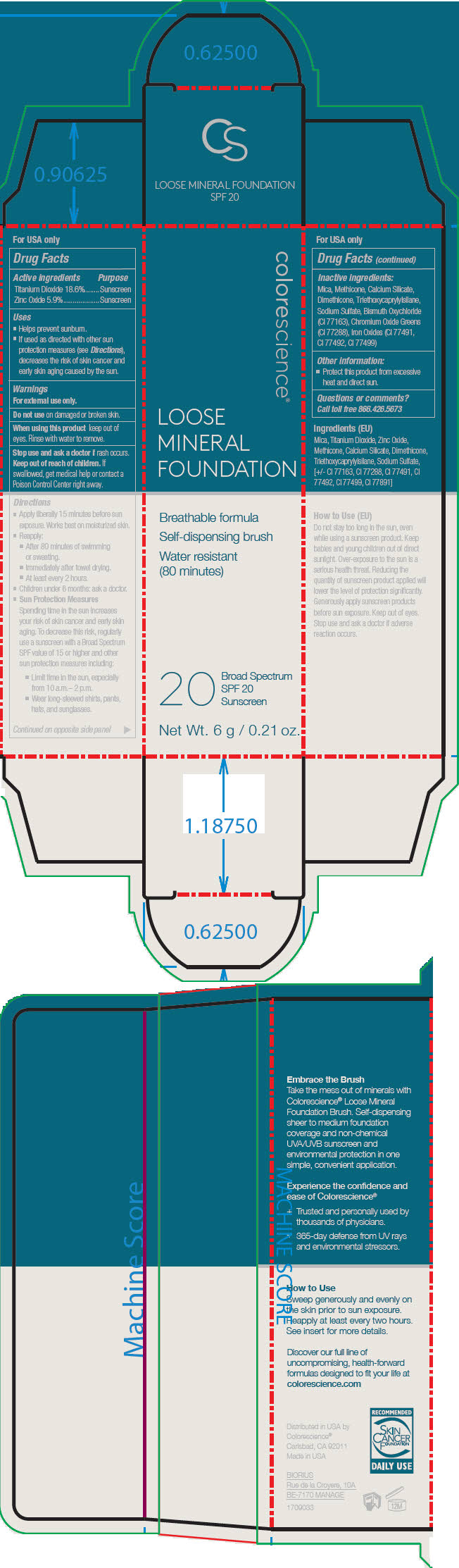 DRUG LABEL: SPF 20 Loose Mineral Foundation
NDC: 68078-000 | Form: POWDER
Manufacturer: Colorescience
Category: otc | Type: HUMAN OTC DRUG LABEL
Date: 20211222

ACTIVE INGREDIENTS: Titanium Dioxide 186 mg/1 g; Zinc Oxide 59 mg/1 g
INACTIVE INGREDIENTS: Mica; Bismuth Oxychloride; Dimethicone; Methicone (20 CST); Triethoxycaprylylsilane; Calcium Silicate; Chromic Oxide; Sodium Sulfate; Ferric Oxide Red; Ferrosoferric Oxide; Ferric Oxide Yellow

SPF 20 Loose Mineral Foundation

Drug Facts

ACTIVE INGREDIENT

Active ingredients | Purpose
Titanium Dioxide 18.6% | Sunscreen
Zinc Oxide 5.9% | Sunscreen

Uses

- Helps prevent sunburn.
- If used as directed with other sun protection measures (see Directions), decreases the risk of skin cancer and early skin aging caused by the sun.

Warnings

For external use only.

Do not use on damaged or broken skin.

When using this product keep out of eyes. Rinse with water to remove.

Stop use and ask a doctor if rash occurs.

Keep out of reach of children. If swallowed, get medical help or contact a Poison Control Center right away.

Directions

- Apply liberally 15 minutes before sun exposure. Works best on moisturized skin.
- Reapply:
  - After 80 minutes of swimming or sweating.
  - Immediately after towel drying.
  - At least every 2 hours.
- Children under 6 months: ask a doctor.
- Sun Protection Measures Spending time in the sun increases your risk of skin cancer and early skin aging. To decrease this risk, regularly use a sunscreen with a Broad Spectrum SPF value of 15 or higher and other sun protection measures including:
  - Limit time in the sun, especially from 10 a.m.– 2 p.m.
  - Wear long-sleeved shirts, pants, hats, and sunglasses.

Inactive ingredients

Mica, Methicone, Calcium Silicate, Dimethicone, Triethoxycaprylylsilane, Sodium Sulfate, Bismuth Oxychloride (CI 77163), Chromium Oxide Greens (CI 77288), Iron Oxides (CI 77491, CI 77492, CI 77499)

Other information

- Protect this product from excessive heat and direct sun.

Questions or comments?

Call toll free 866.426.5673

Manufactured by
Colorescience®
Carlsbad, CA 92011

PRINCIPAL DISPLAY PANEL - 6 g Tube Carton

colorescience®

LOOSE
MINERAL
FOUNDATION

Breathable formula
Self-dispensing brush
Water resistant
(80 minutes)

20
Broad Spectrum
SPF 20
Sunscreen

Net Wt. 6 g / 0.21 oz.